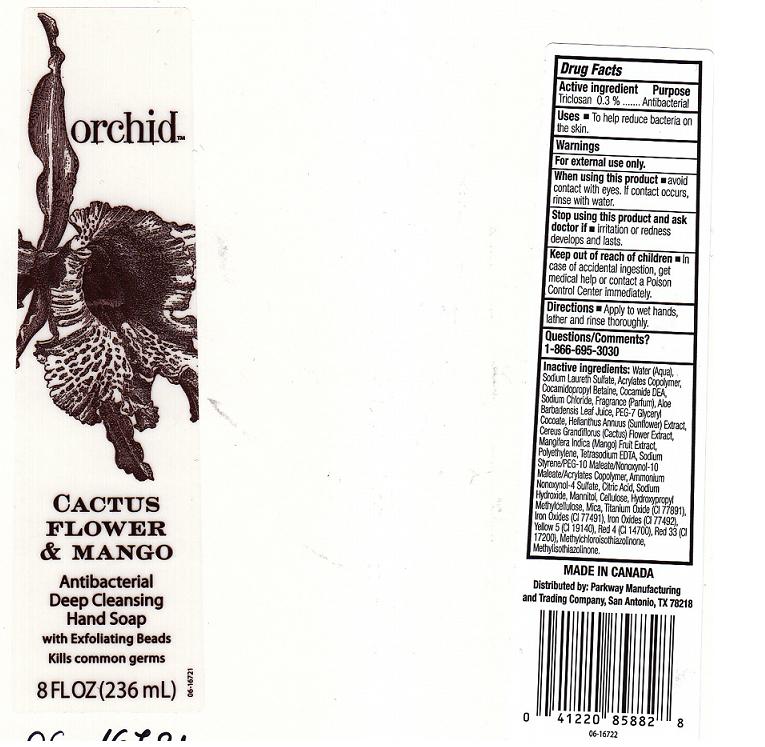 DRUG LABEL: CACTUS FLOWER AND MANGO ANTIBACTERIAL DEEP CLEANSING HAND SP
NDC: 37808-291 | Form: LIQUID
Manufacturer: HEB
Category: otc | Type: HUMAN OTC DRUG LABEL
Date: 20101228

ACTIVE INGREDIENTS: TRICLOSAN 0.3 mL/100 mL
INACTIVE INGREDIENTS: WATER; SODIUM LAURETH SULFATE; CARBOMER COPOLYMER TYPE A; COCAMIDOPROPYL BETAINE; COCO DIETHANOLAMIDE; SODIUM CHLORIDE; ALOE VERA LEAF; GLYCERYL COCOATE; HELIANTHUS ANNUUS FLOWER; SELENICEREUS GRANDIFLORUS FLOWER; MANGO; LOW DENSITY POLYETHYLENE; EDETATE SODIUM; NONOXYNOL-10; AMMONIUM NONOXYNOL-4 SULFATE; ANHYDROUS CITRIC ACID; SODIUM HYDROXIDE; MANNITOL; POWDERED CELLULOSE; HYPROMELLOSES; MICA; TITANIUM DIOXIDE; FERRIC OXIDE RED; FD&C YELLOW NO. 5; FD&C RED NO. 4; D&C RED NO. 33; METHYLCHLOROISOTHIAZOLINONE; METHYLISOTHIAZOLINONE; FERRIC OXIDE YELLOW

DRUG FACTS

ACTIVE INGREDIENT

TRICLOSAN 0.3 PERCENT

PURPOSE

ANTIBACTERIAL

USES

TO HELP REDUCE BACTERIA ON THE SKIN.

WARNINGS

FOR EXTERNAL USE ONLY.

WHEN USING THIS PRODUCT

AVOID CONTACT WITH EYES.IF CONTACT OCCURS, RINSE WITH WATER.

STOP USING THIS PRODUCT AND ASK DOCTOR IF

IRRITATION OR REDNESS DEVELOPS AND LASTS.

KEEP OUT OF REACH OF CHILDREN

IN CASE OF ACCIDENTAL INGESTION, GET MEDICAL HELP OR CONTACT A POISON CONTROL CENTER IMMEDIATELY.

DIRECTIONS

APPLY TO WET HANDS, LATHER AND RINSE THOROUGHLY.

QUESTIONS OR COMMENTS

1-866-695-3030

INACTIVE INGREDIENTS

WATER, SODIUM LAURETH SULFATE, ACRYLATES COPOLYMER, COCAMIDOPROPYL BETAINE, COCAMIDE DEA, SODIUM CHLORIDE, FRAGRANCE, ALOE BARBADENSIS LEAF JUICE, PEG-7 GLYCERYL COCOATE, HELIANTHUS ANNUUS (SUNFLOWER) EXTRACT, CEREUS GRANDIFLORUS (CACTUS) FLOWER EXTRACT, MANGIFERA INDICA (MANGO) FRUIT EXTRACT, POLYETHYLENE, TETRASODIUM EDTA, SODIUM STYRENE/PEG-10 MALEATE/NONOXYNOL-10 MALEATE/ACRYLATES COPOLYMER, AMMONIUM NONOXYNOL-4 SULFATE, CITRIC ACID, SODIUM HYDROXIDE, MANNITOL, CELLULOSE, HYDROXYPROPYL METHYLCELLULOSE, MICA, TITANIUM OXIDE (CI 77891), IRON OXIDES (CI 77491), IRON OXIDES (CI 77492), YELLOW 5 (CI 19140), RED 4 (CI 14700), RED 33 (CI 17200), METHYLCHLOROISOTHIAZOLINONE, METHYLISOTHIAZOLINONE.